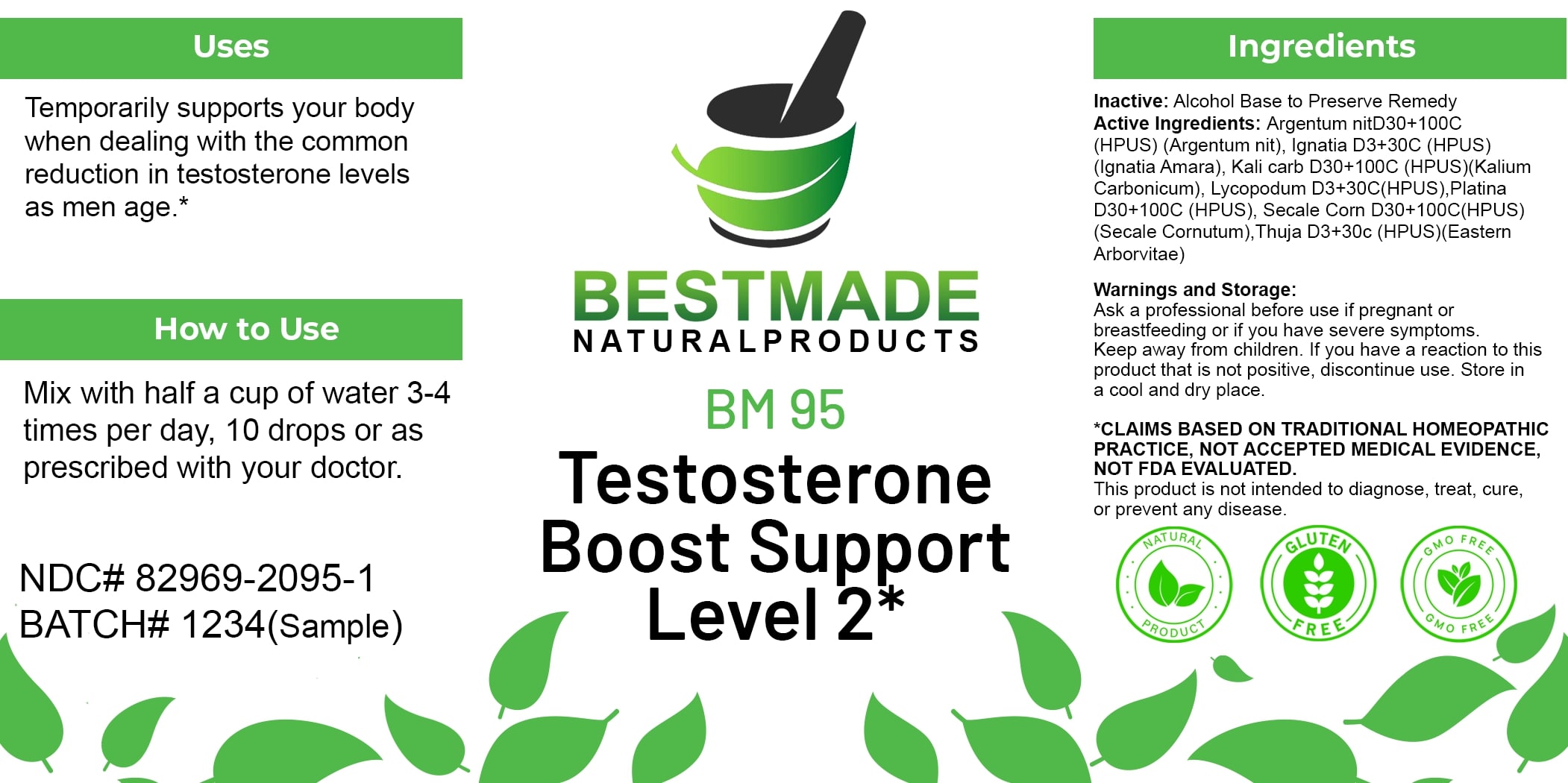 DRUG LABEL: Bestmade Natural Products BM95
NDC: 82969-2095 | Form: LIQUID
Manufacturer: Bestmade Natural Products
Category: homeopathic | Type: HUMAN OTC DRUG LABEL
Date: 20250204

ACTIVE INGREDIENTS: POTASSIUM CARBONATE 30 [hp_C]/30 [hp_C]; SILVER NITRATE 30 [hp_C]/30 [hp_C]; PLATINUM 30 [hp_C]/30 [hp_C]; CLAVICEPS PURPUREA SCLEROTIUM 30 [hp_C]/30 [hp_C]; STRYCHNOS IGNATII SEED 30 [hp_C]/30 [hp_C]; LYCOPODIUM CLAVATUM SPORE 30 [hp_C]/30 [hp_C]; THUJA OCCIDENTALIS LEAFY TWIG 30 [hp_C]/30 [hp_C]
INACTIVE INGREDIENTS: ALCOHOL 30 [hp_C]/30 [hp_C]

BM95

DOSAGE AND ADMINISTRATION

How to Use

Mix with half a cup of water 3-4 times per day, 10 drops or as prescribed with your doctor.

INACTIVE INGREDIENT

Ingredients

Inactive: Alcohol Base to Preserve Remedy

ACTIVE INGREDIENT

Active Ingredients: Argentum Nit 30+100C (HPUS) (Argentum nit), Ignatia 30+30C (HPUS) (Ignatia Amara), Kali carb 30+100C (HPUS) (Kalium Carbonicum), Lycopodium 30+30C (HPUS) (Platina 30+100C (HPUS), Secale Corn 30+100C (HPUS) (Secale Cornutum) Thuja 30+30C (HPUS) (Eastern Arborvitae)

Uses

Temporarily supports your body when dealing with the common reduction in testosterone levels as men age.*

*CLAIMS BASED ON TRADITIONAL HOMEOPATHIC PRACTICE, NOT ACCEPTED MEDICAL EVIDENCE. NOT FDA EVALUATED.

This product is not intended to diagnose, treat, cure, or prevent any disease.

Uses

Temporarily supports your body when dealing with the common reduction in testosterone levels as men age.*

*CLAIMS BASED ON TRADITIONAL HOMEOPATHIC PRACTICE, NOT ACCEPTED MEDICAL EVIDENCE. NOT FDA EVALUATED.

This product is not intended to diagnose, treat, cure, or prevent any disease.

KEEP OUT OF REACH OF CHILDREN

Warnings and Storage:

Ask a professional before use if pregnant or breastfeeding or if you have severe symptoms. Keep away from children. If you have a reaction to this product that is not positive, discontinue use. Store in a cool and dry place.

Warnings and Storage:

Ask a professional before use if pregnant or breastfeeding or if you have severe symptoms. Keep away from children. If you have a reaction to this product that is not positive, discontinue use. Store in a cool and dry place.

*CLAIMS BASED ON TRADITIONAL HOMEOPATHIC PRACTICE, NOT ACCEPTED MEDICAL EVIDENCE. NOT FDA EVALUATED.

This product is not intended to diagnose, treat, cure, or prevent any disease.

Entire package label